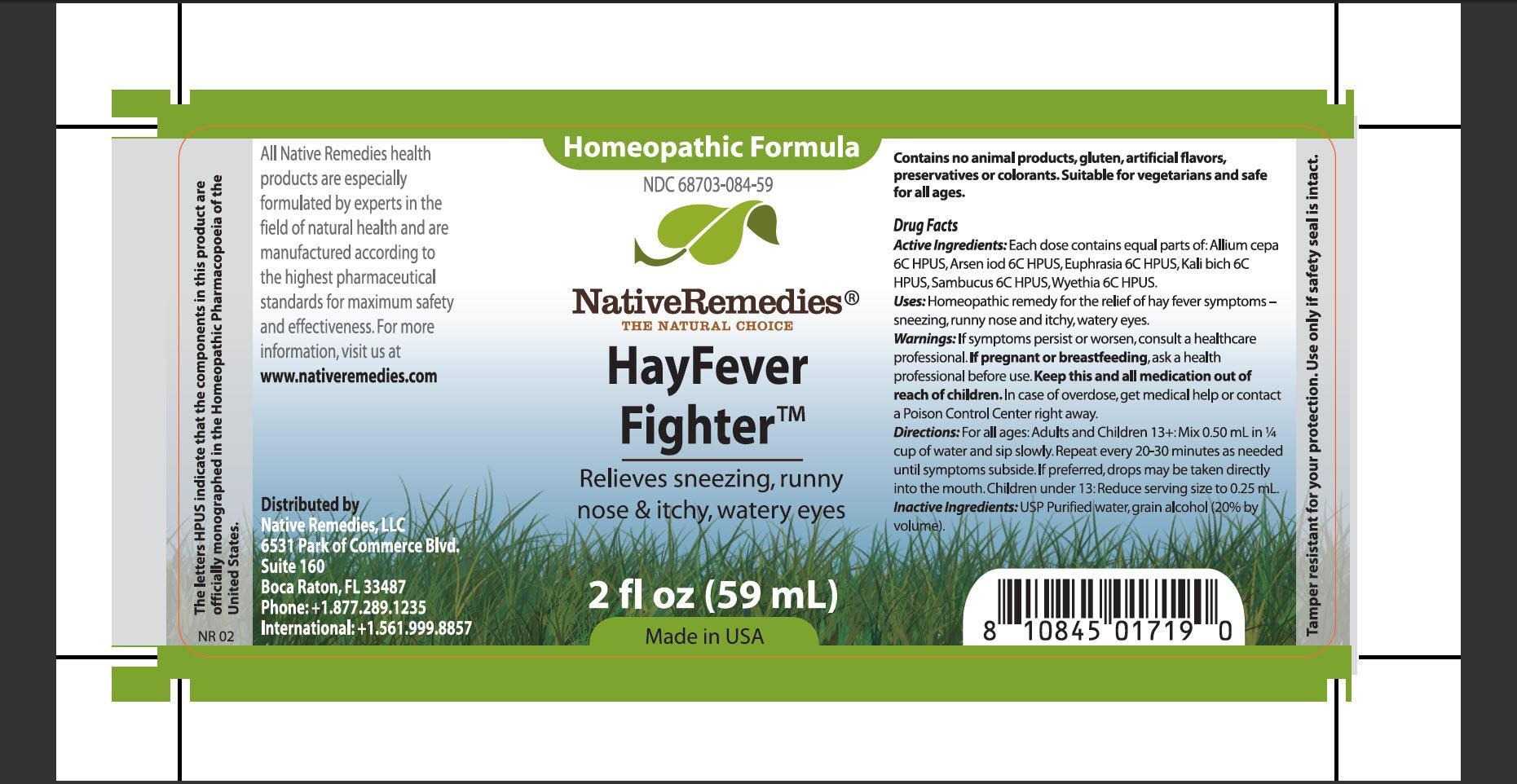 DRUG LABEL: HayFever Fighter
NDC: 68703-084 | Form: TINCTURE
Manufacturer: Native Remedies, LLC
Category: homeopathic | Type: HUMAN OTC DRUG LABEL
Date: 20130411

ACTIVE INGREDIENTS: ONION 6 [hp_C]/1 mL; ARSENIC TRIIODIDE 6 [hp_C]/1 mL; EUPHRASIA STRICTA 6 [hp_C]/1 mL; POTASSIUM DICHROMATE 6 [hp_C]/1 mL; SAMBUCUS CANADENSIS FLOWER 6 [hp_C]/1 mL; WYETHIA HELENIOIDES ROOT 6 [hp_C]/1 mL
INACTIVE INGREDIENTS: WATER; ALCOHOL

HayFever Figther

PURPOSE

Relieves sneezing, runny nose and itchy, watery eyes

ACTIVE INGREDIENT

Active Ingredients: Each dose contains equal parts of: Allium cepa 6C HPUS, Arsen iod 6C HPUS, Euphrasia 6C HPUS, Kali bich 6C HPUS, Sambucus 6C HPUS, Wyethia 6C HPUS

INDICATIONS AND USAGE

Uses: Homeopathic remedy for the relieves of hay fever symptoms sneezing, runny nose and itch, watery eyes

WARNINGS

Warnings: If symptoms persist or worsen, consult a heath care professional

PREGNANCY OR BREAST FEEDING

If pregnant or breastfeeding, ask a health professional before use it

KEEP OUT OF REACH OF CHILDREN

Keep this and all medication out of reach of children

OVERDOSAGE

In case of overdose, get medical help or contact Poison Control Center right away

DOSAGE AND ADMINISTRATION

Directions: For all ages: Adults and Children 13+: Mix 0.50mL in 1/4 cup of water and sip slowly. Repeat every 20-30 minutes as needed until symptoms subside. If preferred, drops may be taken directly into mouth. Children under 13: Reduce serving size to 0.25 mL

INACTIVE INGREDIENT

Inactive Ingredients: USP Purified water, grain alcohol (20% by volume)

PATIENT COUNSELING INFORMATION

The letters HPUS indicate that the component in this product are officially monographed in the Homeopathic Pharmacopoeia of the United States

All Native Remedies health products are especially formulated by expert in the field of natural health and are manufactured according to the highest pharmaceutical standards for maximum safety and effectiveness. For more informations, visit us at www.nativeremedies.com

Distributed by
Native Remedies, LLC
6531 Park of Commerce Blvd.
Suite 160
Boca Raton, FL 33487
Phone:+1.877.289.1235
International:+1.561.999.8857

Contains no animal products, gluten, artificial flavors, preservatives or colorants. Suitable for vegetarians and safe for all ages

STORAGE AND HANDLING

Tamper resistant for your protection. Use only if safety seal is intact